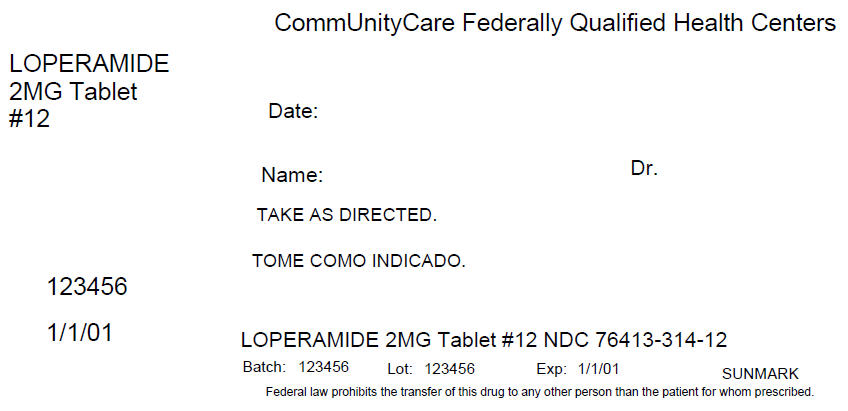 DRUG LABEL: Loperamide hydrochloride
NDC: 76413-314 | Form: TABLET, FILM COATED
Manufacturer: Central Texas Community Health Centers
Category: otc | Type: HUMAN OTC DRUG LABEL
Date: 20160419

ACTIVE INGREDIENTS: LOPERAMIDE HYDROCHLORIDE 2 mg/1 1
INACTIVE INGREDIENTS: ANHYDROUS LACTOSE; CARNAUBA WAX; HYPROMELLOSES; MAGNESIUM STEARATE; CELLULOSE, MICROCRYSTALLINE; POLYETHYLENE GLYCOLS

Loperamide hydrochloride

Active ingredient (in each caplet)

Loperamide HCl 2 mg

Purpose

Anti-diarrheal

Use

controls symptoms of diarrhea, including Travelers' Diarrhea

Warnings

Allergy alert: Do not use if you have ever had a rash or other allergic reaction to loperamide HCl

Do not use

if you have bloody or black stool

Ask a doctor before use if you have

- fever
- mucus in the stool
- a history of liver disease

Ask a doctor or pharmacist before use if you are

taking antibiotics

When using this product

- tiredness, drowsiness or dizziness may occur. Be careful when driving or operating machinery.

Stop use and ask a doctor if

- symptoms get worse
- diarrhea lasts for more than 2 days
- you get abdominal swelling or bulging. These may be signs of a serious condition.

If pregnant or breast-feeding,

ask a health professional before use.

Keep out of reach of children.

In case of overdose, get medical help or contact a Poison Control Center right away. (1-800-222-1222)

Directions

- drink plenty of clear fluids to help prevent dehydration caused by diarrhea
- find right dose on chart. If possible, use weight to dose; otherwise, use age.

adults and children 12 years and over | 2 caplets after the first loose stool; 1 caplet after each subsequent loose stool; but no more than 4 caplets in 24 hours
children 9-11 years (60-95 lbs) | 1 caplet after the first loose stool; 1/2 caplet after each subsequent loose stool; but no more than 3 caplets in 24 hours
children 6-8 years (48-59 lbs) | 1 caplet after the first loose stool; 1/2 caplet after each subsequent loose stool; but no more than 2 caplets in 24 hours
children under 6 years (up to 47 lbs) | ask a doctor

Other information

- store at 20°-25°C (68°-77°F)
- do not use if printed foil under cap is broken or missing
- see end panel for lot number and expiration date

Inactive ingredients

anhydrous lactose, carnauba wax, D&C yellow no. 10 aluminum lake, FD&C blue no. 1 aluminum lake, hypromellose, magnesium stearate, microcrystalline cellulose, polyethylene glycol, pregelatinized starch

PRINCIPAL DISPLAY PANEL - 2 MG Tablet Blister Pack Carton Label

CommUnityCare Federally Qualified Health Centers

LOPERAMIDE
2MG Tablet
#12

Date:

Name:
Dr.

TAKE AS DIRECTED.

123456

1/1/01

LOPERAMIDE 2MG Tablet #12 NDC 76413-314-12

Batch: 123456
Lot: 123456
Exp: 1/1/01
SUNMARK

Federal law prohibits the transfer of this drug to any other person than the patient for whom prescribed.